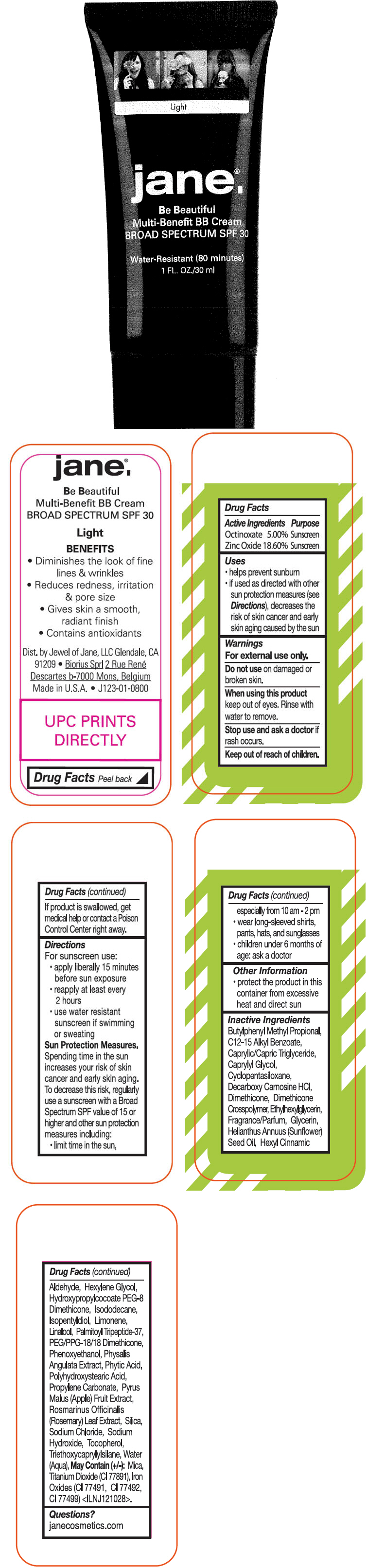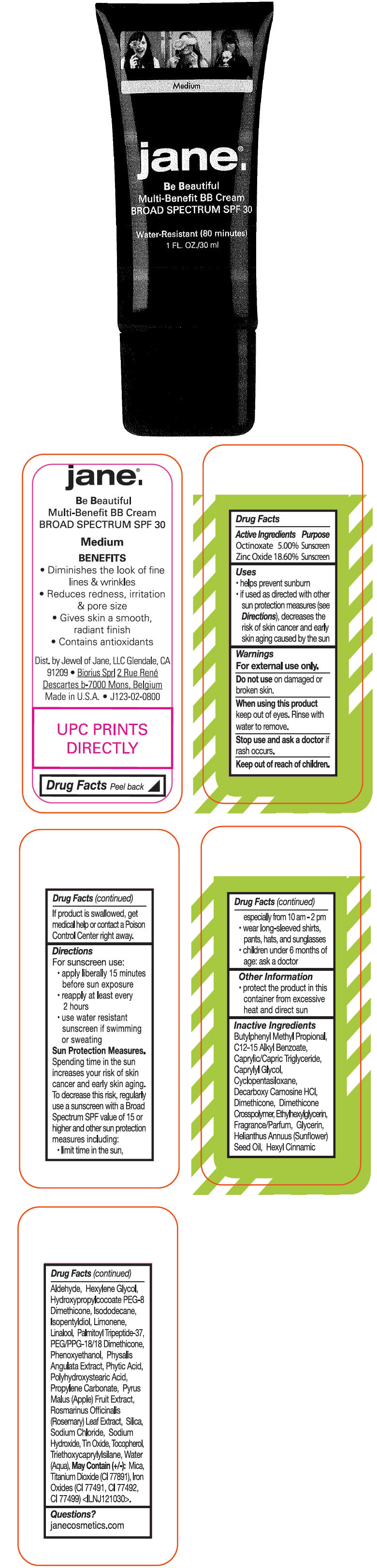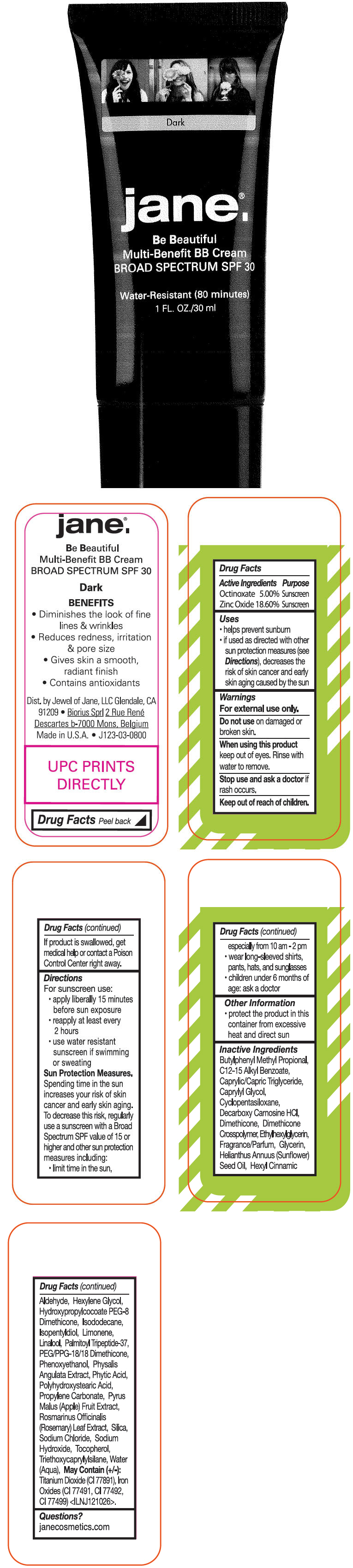 DRUG LABEL: jane Be Beautiful 
NDC: 76049-123 | Form: CREAM
Manufacturer: Stila Styles
Category: otc | Type: HUMAN OTC DRUG LABEL
Date: 20140116

ACTIVE INGREDIENTS: OCTINOXATE 50 mg/1 mL; ZINC OXIDE 186 mg/1 mL
INACTIVE INGREDIENTS: Butylphenyl Methylpropional; Alkyl (C12-15) Benzoate; Medium-Chain Triglycerides; Caprylyl Glycol; Cyclomethicone 5; Decarboxy Carnosine Hydrochloride; Dimethicone; Ethylhexylglycerin; Glycerin; Sunflower Oil; .Alpha.-Hexylcinnamaldehyde; Hexylene Glycol; Hydroxypropylcocoate Peg-8 Dimethicone; Isododecane; Isopentyldiol; Linalool, (+/-)-; PEG/PPG-18/18 Dimethicone; Phenoxyethanol; Physalis Angulata; Fytic Acid; Propylene Carbonate; Apple; Rosemary; Silicon Dioxide; Sodium Chloride; Sodium Hydroxide; Tocopherol; Triethoxycaprylylsilane; Water; Mica; Titanium Dioxide; Ferric Oxide Red; Ferric Oxide Yellow; Ferrosoferric Oxide

jane.® Be Beautiful
Multi-Benefit BB Broad Spectrum SPF 30

Drug Facts

ACTIVE INGREDIENT

Active Ingredients | Purpose
Octinoxate 5.00% | Sunscreen
Zinc Oxide 18.60% | Sunscreen

Uses

- helps prevent sunburn
- if used as directed with other sun protection measures (see Directions), decreases the risk of skin cancer and early skin aging caused by the sun

Warnings

For external use only.

Do not use on damaged or broken skin.

When using this product keep out of eyes. Rinse with water to remove.

Stop use and ask a doctor if rash occurs.

Keep out of reach of children. If product is swallowed, get medical help or contact a Poison Control Center right away.

Directions

For sunscreen use:

- apply liberally 15 minutes before sun exposure
- reapply at least every 2 hours
- use water resistant sunscreen if swimming or sweating

Sun Protection Measures

Spending time in the sun increases your risk of skin cancer and early skin aging. To decrease this risk, regularly use a sunscreen with a Broad Spectrum SPF value of 15 or higher and other sun protection measures including:

- limit time in the sun, especially from 10 am - 2 pm
- wear long-sleeved shirts, pants, hats, and sunglasses
- children under 6 months of age: ask a doctor

Other Information

- protect the product in this container from excessive heat and direct sun

Inactive Ingredients

Butylphenyl Methyl Propional, C12-15 Alkyl Benzoate, Caprylic/Capric Triglyceride, Caprylyl Glycol, Cyclopentasiloxane, Decarboxy Carnosine HCl, Dimethicone, Dimethicone Crosspolymer, Ethylhexylglycerin, Fragrance/Parfum, Glycerin, Helianthus Annuus (Sunflower) Seed Oil, Hexyl Cinnamic Aldehyde, Hexylene Glycol, Hydroxypropylcocoate PEG-8 Dimethicone, Isododecane, Isopentyldiol, Limonene, Linalool, Palmitoyl Tripeptide-37, PEG/PPG-18/18 Dimethicone, Phenoxyethanol, Physalis Angulata Extract, Phytic Acid, Polyhydroxystearic Acid, Propylene Carbonate, Pyrus Malus (Apple) Fruit Extract, Rosmarinus Officinalis (Rosemary) Leaf Extract, Silica, Sodium Chloride, Sodium Hydroxide, Tin Oxide, Tocopherol, Triethoxycaprylylsilane, Water (Aqua), May Contain (+/-): Mica, Titanium Dioxide (CI 77891), Iron Oxides (CI 77491, CI 77492, CI 77499) <ILNJ121030>.

Questions?

janecosmetics.com

Dist. by Jewel of Jane, LLC Glendale, CA
91209 • Biorius Sprl 2 Rue René
Descartes b-7000 Mons, Belgium

PRINCIPAL DISPLAY PANEL - 30 ml Tube - Light

Light

jane.®

Be Beautiful
Multi-Benefit BB Cream
BROAD SPECTRUM SPF 30

Water-Resistant (80 minutes)
1 FL. OZ./30 ml

PRINCIPAL DISPLAY PANEL - 30 ml Tube - Medium

Medium

jane.®

Be Beautiful
Multi-Benefit BB Cream
BROAD SPECTRUM SPF 30

Water-Resistant (80 minutes)
1 FL. OZ./30 ml

PRINCIPAL DISPLAY PANEL - 30 ml Tube - Dark

Dark

jane.®

Be Beautiful
Multi-Benefit BB Cream
BROAD SPECTRUM SPF 30

Water-Resistant (80 minutes)
1 FL. OZ./30 ml